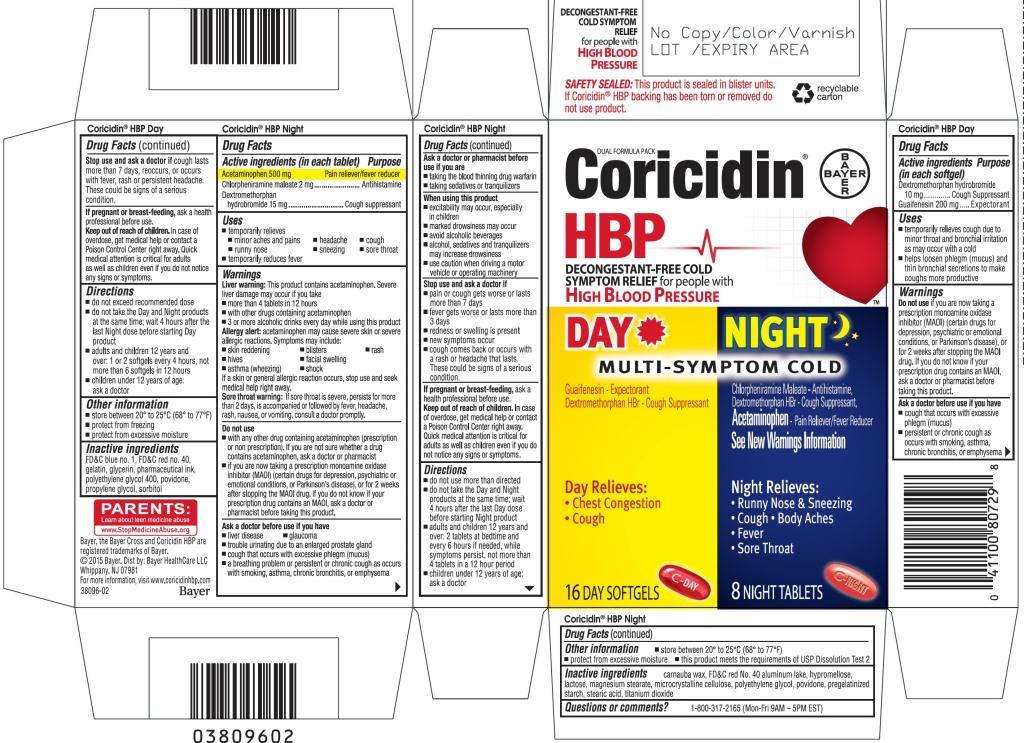 DRUG LABEL: Coricidin HBP
NDC: 11523-4765 | Form: KIT | Route: ORAL
Manufacturer: Bayer HealthCare LLC.
Category: otc | Type: HUMAN OTC DRUG LABEL
Date: 20251205

ACTIVE INGREDIENTS: DEXTROMETHORPHAN HYDROBROMIDE 10 mg/1 1; GUAIFENESIN 200 mg/1 1; ACETAMINOPHEN 500 mg/1 1; CHLORPHENIRAMINE MALEATE 2 mg/1 1; DEXTROMETHORPHAN HYDROBROMIDE 15 mg/1 1
INACTIVE INGREDIENTS: FD&C BLUE NO. 1; FD&C RED NO. 40; GELATIN; POLYETHYLENE GLYCOL 400; POVIDONE; PROPYLENE GLYCOL; SORBITOL; CARNAUBA WAX; FD&C RED NO. 40; ALUMINUM OXIDE; HYPROMELLOSES; LACTOSE; MAGNESIUM STEARATE; CELLULOSE, MICROCRYSTALLINE; PROPYLENE GLYCOL; POVIDONE; STEARIC ACID; TITANIUM DIOXIDE

Coricidin HBP
Day and Night Multi-Symptom Cold

Coricidin HBP Day

Drug Facts

ACTIVE INGREDIENT

Active ingredients (in each softgel) | Purpose
Dextromethorphan hydrobromide 10 mg | Cough Suppressant
Guaifenesin 200 mg | Expectorant

Uses

- temporarily relieves cough due to minor throat and bronchial irritation as may occur with a cold
- helps loosen phlegm (mucus) and thin bronchial secretions to make coughs more productive

Warnings

Do not use if you are now taking a prescription monoamine oxidase inhibitor (MAOI) (certain drugs for depression, psychiatric or emotional conditions, or Parkinson's disease), or for 2 weeks after stopping the MAOI drug. If you do not know if your prescription drug contains an MAOI, ask a doctor or pharmacist before taking this product.

Ask a doctor before use if you have

- cough that occurs with excessive phlegm (mucus)
- persistent or chronic cough as occurs with smoking, asthma, chronic bronchitis, or emphysema

Stop use and ask a doctor if cough lasts more than 7 days, reoccurs, or occurs with fever, rash or persistent headache. These could be signs of a serious condition.

PREGNANCY OR BREAST FEEDING

If pregnant or breast-feeding, ask a health professional before use.

Keep out of reach of children. In case of overdose, get medical help or contact a Poison Control Center right away. Abuse of this product can lead to serious injury.

Directions

- do not exceed recommended dose
- do not take the Day and Night products at the same time; wait 4 hours after the last Night dose before starting Day product
- adults and children 12 years and over: 1 or 2 softgels every 4 hours, not more than 6 softgels in 12 hours
- children under 12 years of age: ask a doctor

Other Information

- store between 20° to 25°C (68° to 77°F)
- protect from freezing
- protect from excessive moisture

Inactive Ingredients

FD&C blue no. 1, FD&C red no. 40, gelatin, glycerin, pharmaceutical ink, polyethylene glycol 400, povidone, propylene glycol, sorbitol

Coricidin HBP Night

Drug Facts

ACTIVE INGREDIENT

Active ingredients (in each tablet) | Purpose
Acetaminophen 500 mg | Pain reliever/fever reducer
Chlorpheniramine maleate 2 mg | Antihistamine
Dextromethorphan hydrobromide 15 mg | Cough Suppressant

Uses

- temporarily relieves
  - minor aches and pains
  - headache
  - cough
  - runny nose
  - sneezing
- temporarily reduces fever

Warnings

Liver Warning

This product contains acetaminophen.

Sever liver damage may occur if you take

- more than 4 tablets in 12 hours
- with other drugs containing acetaminophen
- 3 or more alcoholic drinks every day while using this product

Do not use

- with any other drug containing acetaminophen (prescription or non prescription). If you are not sure whether a drug contains acetaminophen, ask a doctor or pharmacist.
- if you are now taking a prescription monoamine oxidase inhibitor (MAOI) (certain drugs for depression, psychiatric or emotional conditions, or Parkinson's disease), or for 2 weeks after stopping the MAOI drug. If you do not know if your prescription drug contains a MAOI, ask a doctor or pharmacist before taking this product.

Ask a doctor before use if you have

- liver disease
- glaucoma
- trouble urinating due to an enlarged prostate gland
- cough that occurs with excessive phlegm (mucus)
- a breathing problem or persistent or chronic cough as occurs with smoking, asthma, chronic bronchitis, or emphysema

Ask a doctor or pharmacist before use if you are

- taking the blood thinning drug warfarin
- taking sedatives or tranquilizers

When using this product

- excitability may occur, especially in children
- marked drowsiness may occur
- avoid alcoholic beverages
- alcohol, sedatives and tranquilizers may increase drowsiness
- use caution when driving a motor vehicle or operating machinery

Stop use and ask a doctor if

- pain or cough gets worse or lasts more than 7 days
- fever gets worse or lasts more than 3 days
- redness or swelling is present
- new symptoms occur
- cough comes back or occurs with a rash or headache that lasts. These could be signs of a serious condition.

PREGNANCY OR BREAST FEEDING

If pregnant or breast-feeding, ask a health professional before use.

Keep out of reach of children. Abuse of this product can lead to serious injury.

Overdose Warning

Taking more than the recommended dose may cause liver damage. In case of overdose, get medical help or contact a Poison Control Center right away. Quick medical attention is critical for adults as well as children even if you do not notice any signs or symptoms.

Directions

- do not use more than directed (see overdose warning)
- do not take the Day and Night products at the same time; wait 4 hours after the last Day dose before starting Night product
- adults and children 12 years and over: 2 tablets at bedtime and every 6 hours if needed, while symptoms persist, not more than 4 tablets in a 12 hour period
- children under 12 years of age: ask a doctor

Other Information

- store between 20° to 25°C (68° to 77°F)
- protect from excessive moisture
- this product meets the requirements of USP Dissolution Test 2

Inactive Ingredients

carnauba wax, FD&C red No. 40 aluminum lake, hypromellose, lactose, magnesium stearate, microcrystalline cellulose, polyethylene glycol, povidone, pregelatinized starch, stearic acid, titanium dioxide

Questions or comments?

Call 1-800-317-2165 (MoN-Fri 9AM-5PM EST)

PRINCIPAL DISPLAY PANEL - Kit Carton

DUAL FORMULA PACK
Coricidin®
HBP

Decongestant-free COLD RELIEF for people
with HIGH BLOOD PRESSURE

DAY

MULTI-SYMPTOM COLD

Guaifenesin - Expectorant
Dextromethorphan HBr - Cough Suppressant

Day Relieves:

- Chest Congestion
- Cough

16 DAY SOFTGELS

NIGHT

Chlorpheniramine Maleate - Antihistamine,
Dextromethorphan HBr - Cough Suppressant,
Acetaminophen - Pain Reliever/Fever Reducer

See New Warnings Information

Night Relieves:

- Runny Nose & Sneezing
- Cough • Body Aches
- Fever

8 NIGHT TABLETS